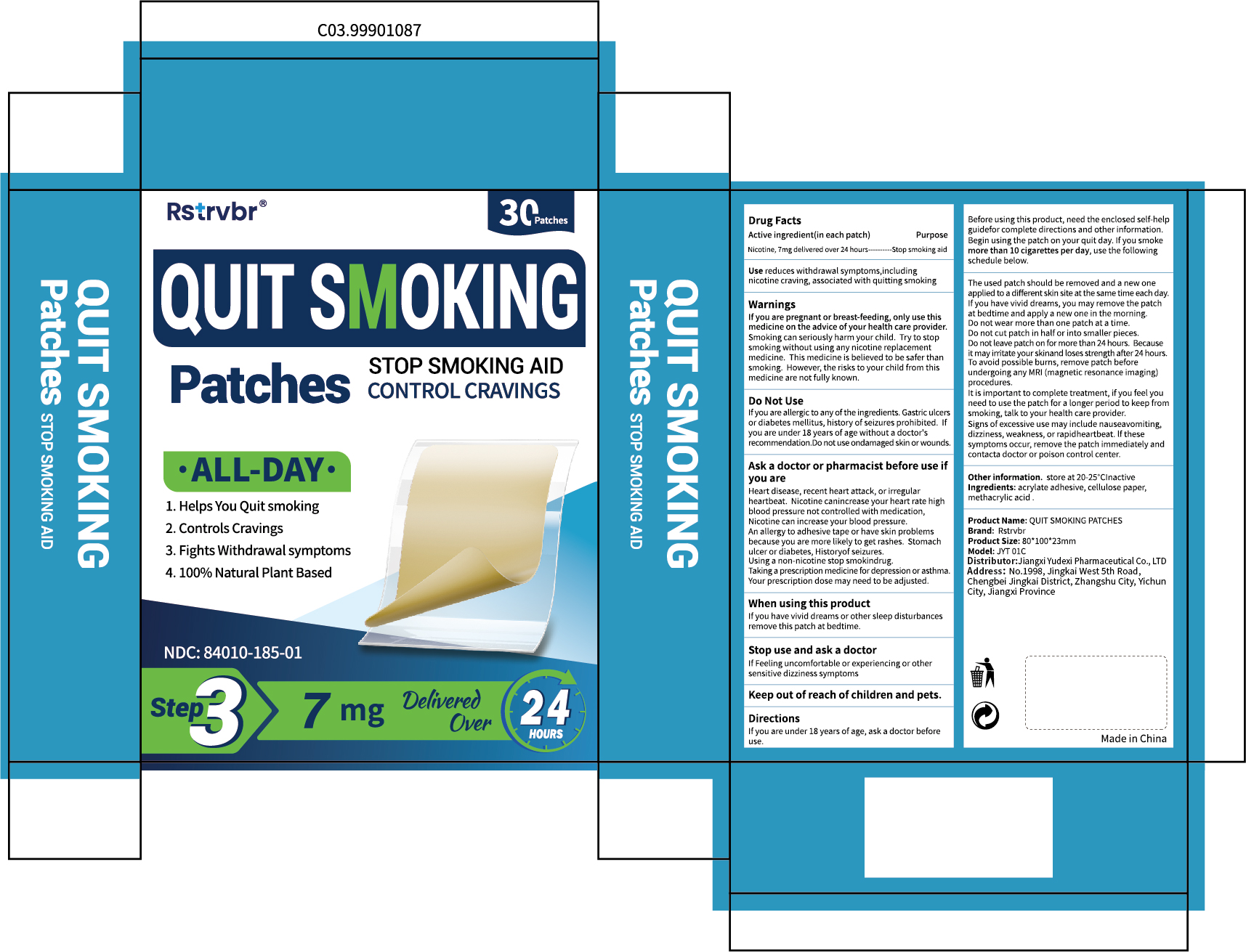 DRUG LABEL: Rstrvbr QUIT SMOKING
NDC: 85248-132 | Form: PATCH
Manufacturer: Jiangxi Yudexi Pharmaceutical Co., LTD
Category: otc | Type: HUMAN OTC DRUG LABEL
Date: 20260209

ACTIVE INGREDIENTS: NICOTINE 7 mg/100 1
INACTIVE INGREDIENTS: METHACRYLIC ACID; 2-HYDROXYETHYL ACRYLATE; POWDERED CELLULOSE

85248-132

Active Ingredient

Nicotine,7mg delivered over 24 hours

Purpose

stop smoking aid

Use

reduces withdrawal symptoms,including nicotine craving,associated with quitting smoking

Warnings

If you are pregnant or breast-feeding, only use this medicine on the advice of your health care provider.Smoking can seriously harm your child. Try to stop smoking without using any nicotine replacement medicine, This medicine is believed to be safer than smoking.However, the risks to your child from this medicine are not fully known.

Do not use

If you are allergic to any of the ingredients. ·Gastric ulcers or diabetes mellitus, history of seizures prohibited. · lf you are under 18 years of age without a doctor's recommendation. · Do not use on damaged skin or wounds.

When Using

If you have vivid dreams or other sleep disturbances remov this patch at bedtime.

Stop Use

If Feeling uncomfortable or experiencing or other sensitive dizziness symptoms

Ask Doctor

Heart disease, recent heart attack, or irrepular heartbeat. Nicotine canincrease your heart high blood pressure not controlled with medication,Nicotine can increase your blood pressure.
An allergy to adhesive tape or have skin problems because you are more likely to get rashes, Stomach
ulcer or diabetes,History of seizures Using a non-nicotine stop smokindrug.Taking a prescription medicine for depression or asthma Your prescription dose may need to be adjusted

Keep Oot Of Reach Of Children

Keep out of reach of children and pets

Directions

lf you are under 18 years of age, ask a doctor before uSe, Beore using this product, need the enclosed self-help guidefor complete directions and other information.Bepin using the patch on your quit day. lf you smoke more than 10 cigarettes per day, use the following schedule below. The used patch should be removed and a new one applied to a different skin site at the same time each day.If you have vivid dreams, you may remove the patch at bedtime and apply a new one in the morninp.Do not wear more than one patch at a time.Dnot cut patch in half or into smaller pieces.Do not leave patch on for more than 24 hours. Because it may irritate your skinand loses strength after 24 hours.To avoid possible bums,remove patch before undergoing any MRl (magnetic resonance imaging)procedures.
It is important to complete treatrent, if you feel you need to use the patch for a longer period to keep from smoking, talk to your health care provider.Signs of excessive use may include nauseavomiting,dizzines,weakness, or rapidheartbeat. lf these Symptoms occur, remove the patch immediately and contata doctor or poison control center.

Other information

store at 20-25℃ lnactive

Inactive ingredients

acrylate adhesive，cellulose paper，methacrylic acid .